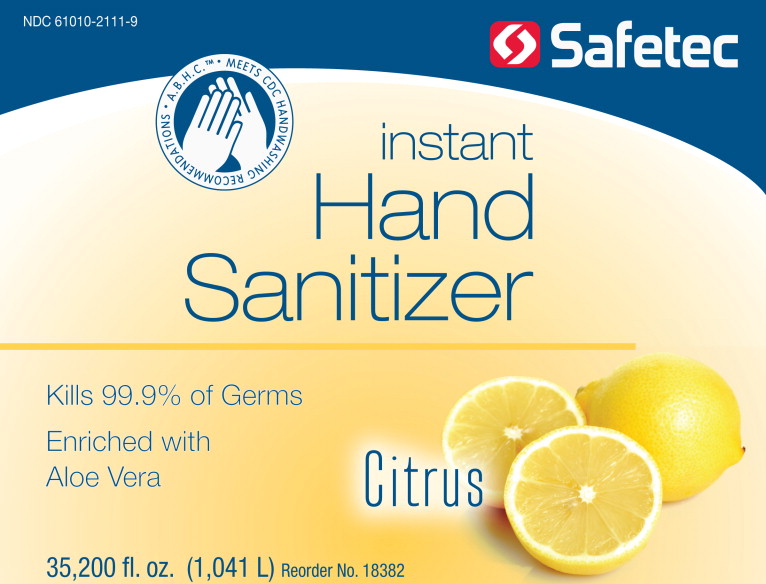 DRUG LABEL: A.B.H.C. Instant Hand Sanitizer Citrus Scent
NDC: 61010-2111 | Form: GEL
Manufacturer: Safetec of America, Inc.
Category: otc | Type: HUMAN OTC DRUG LABEL
Date: 20100421

ACTIVE INGREDIENTS: Alcohol 665 mL/1 L
INACTIVE INGREDIENTS: Aloe; water

A.B.H.C. INSTANT HAND SANITIZER

Drug Facts

Active ingredient

Ethyl Alcohol 66.5%

Purpose

Antiseptic

Uses

- for handwashing to decrease bacteria on skin whenever soap and water handwashing is not readily available
- helps prevent the risk of cross-contamination of bacteria that potentially can cause disease or infection
- recommended for repeated use

Warnings

For external use only. Flammable, keep away from fire or flame

When using this product

- do not get into eyes. If contact occurs, rinse eyes thoroughly with water

Stop use and ask doctor if

- irritation and redness develop and persists for more than 72 hours

Keep out of reach of children. If swallowed, get medical help or contact a Poison Control Center right away

Directions

- place a small amount into one hand
- spread over both hands and wrist
- rub into the skin until dry
- do not wipe off; no rinsing required

Inactive ingredients

aloe vera, carbomer, fragrance, purified water, triethanolamine

Manufactured by SAFETEC OF AMERICA, Inc. Buffalo, NY 14215 800-456-7077 www.safetec.com

PACKAGE LABEL - PRINCIPAL DISPLAY PANEL – A.B.H.C. INSTANT HAND SANITIZER Citrus Scent

NDC 61010-2111-9

SAFETEC A.B.H.C. INSTANT HAND SANITIZER Kills 99.9% of Germs, Enriched with Aloe vera 275 Gallons (1041 L)

Manufactured by Safetec of America, Inc. Buffalo, NY 14215
www.safetec.com 800-456-7077